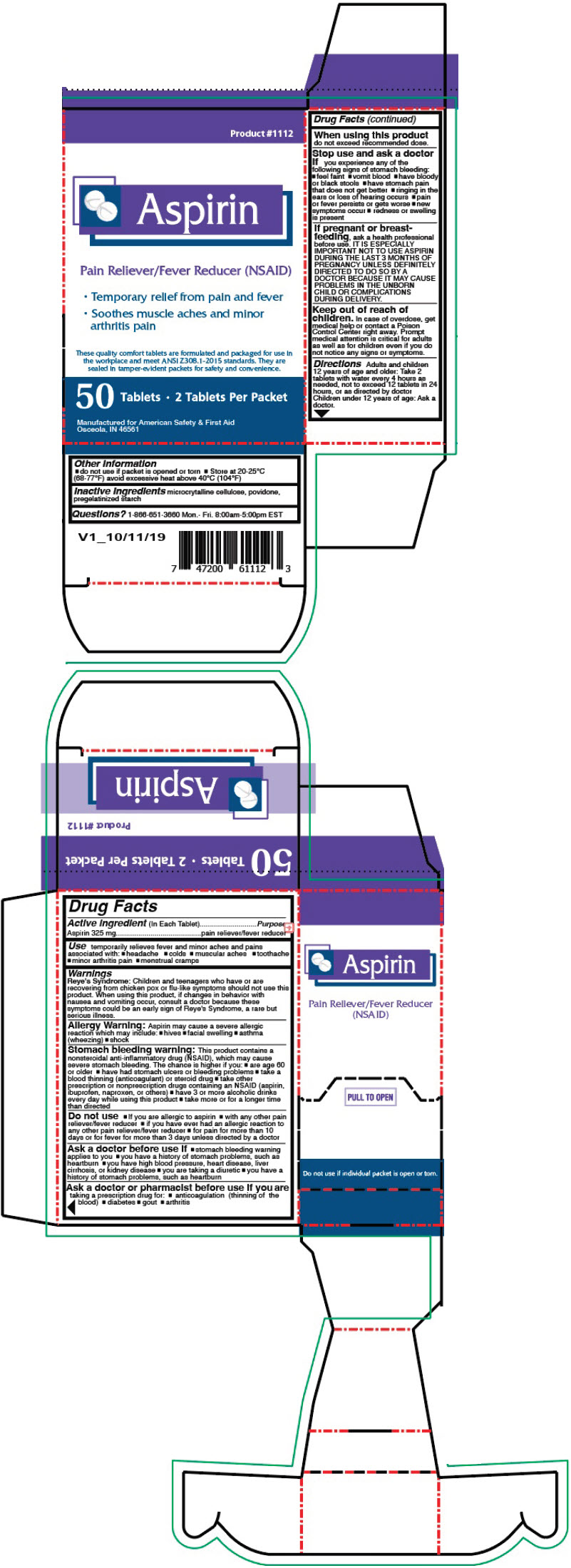 DRUG LABEL: Aspirin 50 CT
NDC: 73598-1112 | Form: TABLET
Manufacturer: JHK Inc dba American Safety & First Aid
Category: otc | Type: HUMAN OTC DRUG LABEL
Date: 20240426

ACTIVE INGREDIENTS: ASPIRIN 325 mg/1 1
INACTIVE INGREDIENTS: MICROCRYSTALLINE CELLULOSE; POVIDONE, UNSPECIFIED; STARCH, CORN

Aspirin 50 CT

Drug Facts

Active ingredient (In Each Tablets)

Aspirin 325 mg

Purpose

pain reliever/fever reducer

Use

temporarily relieves fever and minor aches and pains associated with:

- headache
- colds
- muscular aches
- toothache
- minor arthritis pain
- menstrual cramps

Warnings

Reye's Syndrome

Children and teenagers who have or are recovering from chicken pox or flu-like symptoms should not use this product. When using this product, if changes in behavior with nausea and vomiting occur, consult a doctor because these symptoms could be an early sign of Reye's Syndrome, a rare but serious illness.

Allergy Warning

Aspirin may cause a severe allergic reaction which may include:

- hives
- facial swelling
- asthma (wheezing)
- shock

Stomach bleeding warning

This product contains a nonsteroidal anti-inflammatory drug (NSAID), which may cause severe stomach bleeding. The chance is higher if you:

- are age 60 or older
- have had stomach ulcers or bleeding problems
- take a blood thinning (anticoagulant) or steroid drug
- take other prescription or nonprescription drugs containing an NSAID (aspirin, ibuprofen, naproxen, or others)
- have 3 or more alcoholic drinks every day while using this product
- take more or for a longer time than directed

Do not use

- If you are allergic to aspirin
- with any other pain reliever/fever reducer
- if you have ever had an allergic reaction to any other pain reliever/fever reducer
- for pain for more than 10 days or for fever for more than 3 days unless directed by a doctor

Ask a doctor before use if

- stomach bleeding warning applies to you
- you have a history of stomach problems, such as heartburn
- you have high blood pressure, heart disease, liver cirrhosis, or kidney disease
- you are taking a diuretic
- you have a history of stomach problems, such as heartburn

Stop use and ask a doctor if you experience any of the following signs of stomach bleeding:

- feel faint
- vomit blood
- have bloody or black stools
- have stomach pain that does not get better
- pain gets worse or lasts more than 10 days
- fever gets worse or lasts more than 3 days
- redness or swelling is present in the painful area
- any new symptoms appear

Ask a doctor or pharmacist before use if you are taking a prescription drug for:

- anticoagulation (thinning of the blood)
- diabetes
- gout
- arthritis

When using this product do not exceed recommended dose.

Stop use and ask a doctor if you experience any of the following signs of stomach bleeding:

- feel faint
- vomit blood
- have bloody or black stools
- have stomach pain that does not get better
- ringing in the ears or loss of hearing occurs
- pain or fever persists or gets worse
- new symptoms occur
- redness or swelling is present

PREGNANCY OR BREAST FEEDING

If pregnant or breast-feeding, ask a health professional before use. IT IS ESPECIALLY IMPORTANT NOT TO USE ASPIRIN DURING THE LAST 3 MONTHS OF PREGNANCY UNLESS DEFINITELY DIRECTED TO DO SO BY A DOCTOR BECAUSE IT MAY CAUSE PROBLEMS IN THE UNBORN CHILD OR COMPLICATIONS DURING DELIVERY.

Keep out of reach of children. In case of overdose, get medical help or contact a Poison Control Center right away. Prompt medical attention is critical for adults as well as for children even if you do not notice any signs or symptoms.

Directions

Adults and children 12 years of age and older: Take 2 tablets with water every 4 hours as needed, not to exceed 12 tablets in 24 hours, or as directed by doctor Children under 12 years of age: Ask a doctor.

Other Information

- do not use if packet is opened or torn
- Store at 20-25°C (68-77°F) avoid excessive heat above 40°C (104°F)

Inactive Ingredients

microcrytalline cellulose, povidone, pregelatinized starch

Questions?

1-866-651-3660 Monday-Friday 8:00am-5:00pm EST

PRINCIPAL DISPLAY PANEL - 50 Tablet Packet Box

Product #1112

Aspirin

Pain Reliever/Fever Reducer (NSAID)

- Temporary relief from pain and fever
- Soothes muscle aches and minor
  arthritis pain

These quality comfort tablets are formulated and packaged for use in
the workplace and meet ANSI Z308.1-2015 standards. They are
sealed in tamper-evident packets for safety and convenience.

50 Tablets • 2 Tablets Per Packet

Manufactured for American Safety & First Aid
Osceola, IN 46561